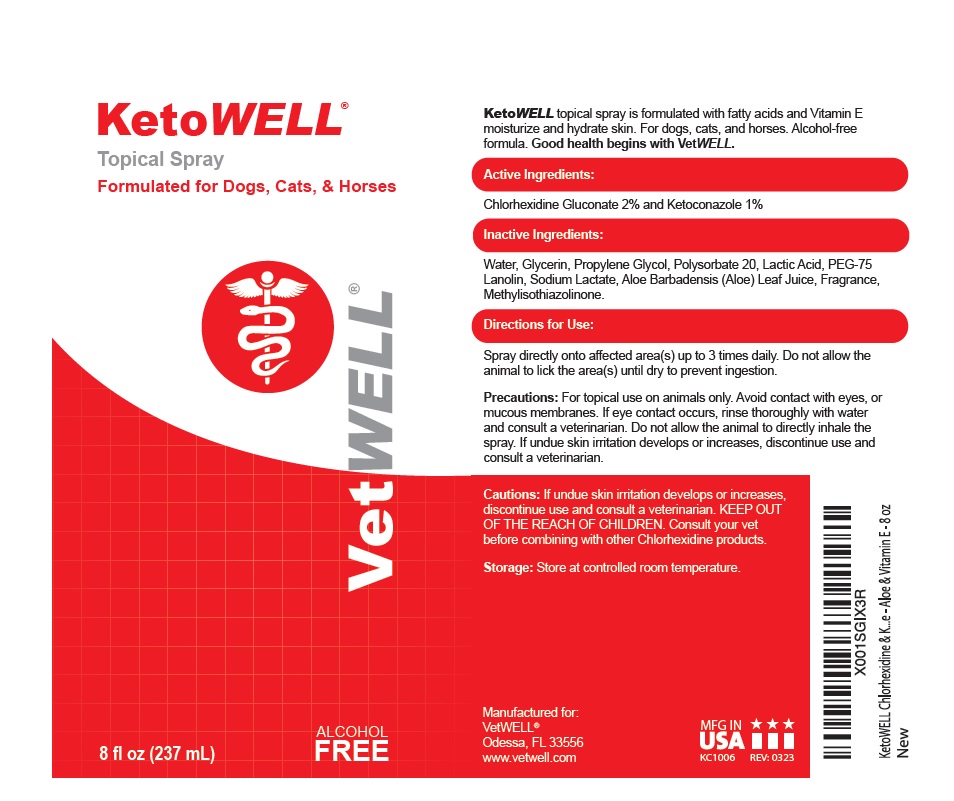 DRUG LABEL: KetoWELL
NDC: 86090-008 | Form: SPRAY
Manufacturer: Pet MD Brands, LLC
Category: animal | Type: OTC ANIMAL DRUG LABEL
Date: 20230907

ACTIVE INGREDIENTS: CHLORHEXIDINE GLUCONATE 2 g/100 mL; KETOCONAZOLE 1 g/100 mL
INACTIVE INGREDIENTS: WATER; GLYCERIN; PROPYLENE GLYCOL; POLYSORBATE 20; LACTIC ACID, UNSPECIFIED FORM; PEG-75 LANOLIN; SODIUM LACTATE; ALOE VERA LEAF; METHYLISOTHIAZOLINONE

KetoWELL® Spray

Active Ingredients:

Chlorhexidine Gluconate 2% and Ketoconazole 1%

INDICATIONS AND USAGE

KetoWELL topical spray is formulated with fatty acids and Vitamin E moisturize and hydrate skin. For dogs, cats, and horses. Alcohol-free formula. Good health begins with VetWELL.

Inactive Ingredients:

Water, Glycerin, Propylene Glycol, Polysorbate 20, Lactic Acid, PEG-75 Lanolin, Sodium Lactate, Aloe Barbadensis (Aloe) Leaf Juice, Fragrance, Methylisothiazolinone.

Directions for Use:

Spray directly onto affected area(s) up to 3 times daily. Do not allow the animal to lick the area(s) until dry to prevent ingestion.

Precautions:

For topical use on animals only. Avoid contact with eyes, or mucous membranes. If eye contact occurs, rinse thoroughly with water and consult a veterinarian. Do not allow the animal to directly inhale the spray.

Cautions:

If undue skin irritation develops or increases, discontinue use and consult a veterinarian. KEEP OUT OF THE REACH OF CHILDREN. Consult your vet before combining with other Chlorhexidine products.

Storage:

Store at controlled room temperature.

Formulated for Dogs, Cats, & Horses

ALCOHOL FREE

Manufactured for:
VetWELL®
Odessa, FL 33556
www.vetwell.com

MFG IN USA